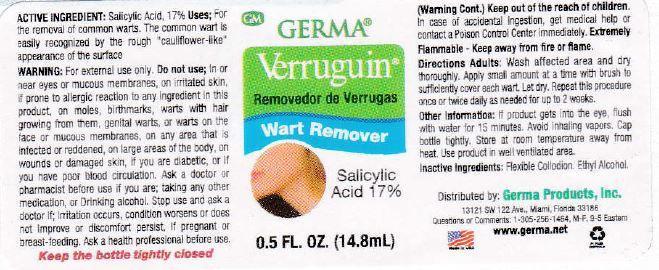 DRUG LABEL: Verruguin
NDC: 59561-901 | Form: GEL
Manufacturer: Caribe Natural, Inc
Category: otc | Type: HUMAN OTC DRUG LABEL
Date: 20150506

ACTIVE INGREDIENTS: SALICYLIC ACID 17 g/100 g
INACTIVE INGREDIENTS: PYROXYLIN; ETHER; ALCOHOL; ISOPROPYL ALCOHOL

ACTIVE INGREDIENT: Salicylic Acid 17%

PURPOSE

Uses: For the removal of common warts. The common wart is easily recognized by the rough "cauliflower-like" appearance of the surface.

KEEP OUT OF REACH OF CHILDREN

Keep out of the reach of children. In case of accidental ingestion, get medical help or contact a Poison Control Center immediately.

INDICATIONS AND USAGE

Verruguin

Removedor de Verrugas

Wart Remover

Salicylic Acid 17%

DOSAGE AND ADMINISTRATION

Directions Adults: Wash affected area and dry thoroughly. Apply small amount at a time with brush to sufficiently cover each wart. Let dry. Repeat this procedure once or twice daily as needed for up to 2 weeks.

WARNINGS

WARNING: For external use only. Do not use; in or near eyes or mucous membranes, on irritated skin, if prone to allergic reaction to any ingredient in this product, on moles, birthmarks, warts with hair growing from them, genital warts, or warts on the face or mucous membranes, on any area that is infected or reddened, on large areas of the body, on wounds or damaged skin, if you are diabetic, or if you have poor blood circulation. Ask a doctor or pharmacist before use if you are; taking any other medication, or Drinking alcohol. Stop use and ask a doctor if; irritation occurs, condition worsens or does not improve or discomfort persist. If pregnant or breast-feeding. Ask a health professional before use.

Keep the bottle tightly closed

Inactive Ingredients: flexible collodion, ethyl alcohol.